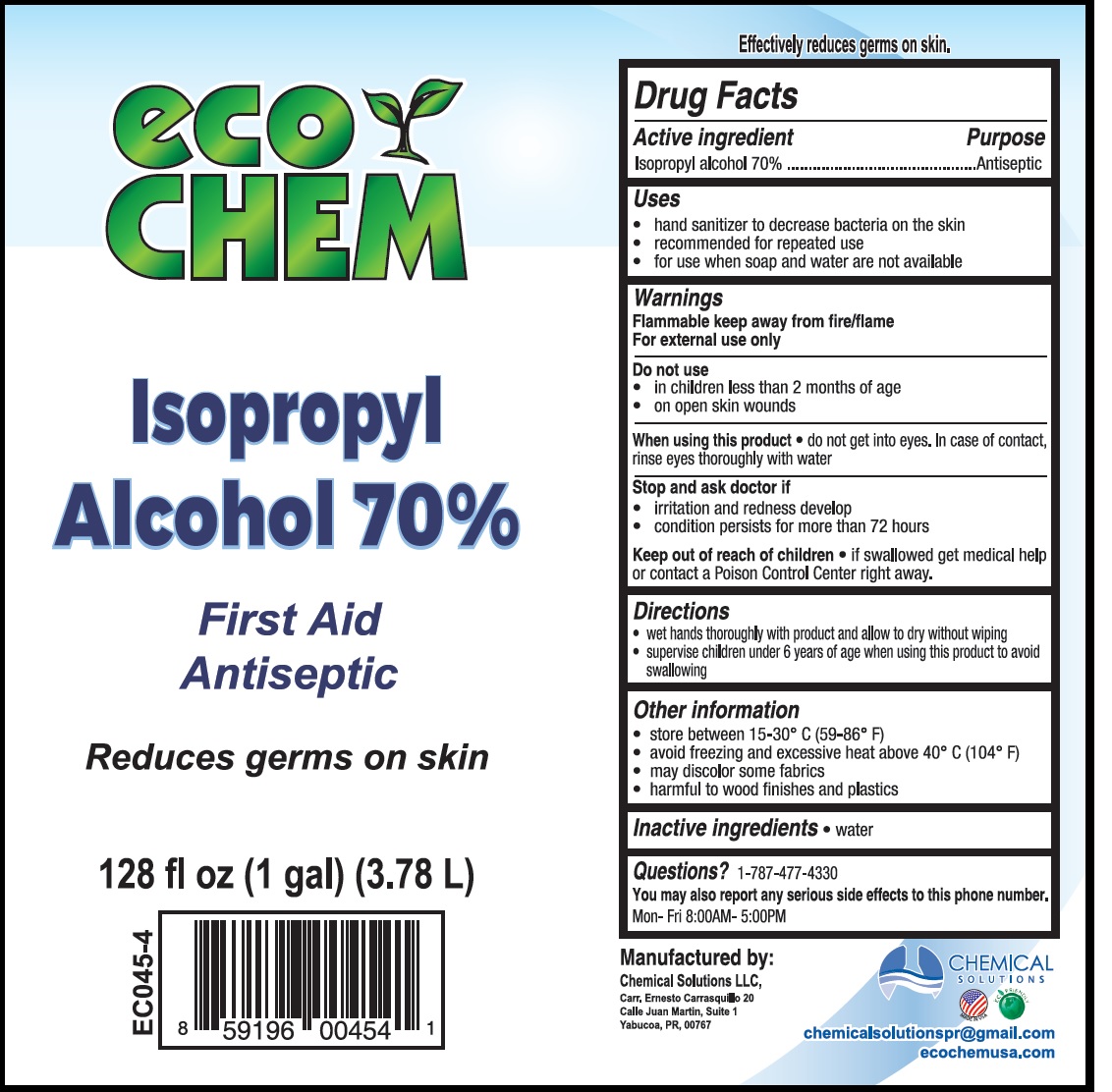 DRUG LABEL: Eco Chem isopropyl alcohol 70
NDC: 75650-003 | Form: LIQUID
Manufacturer: Chemical Solutions, LLC
Category: otc | Type: HUMAN OTC DRUG LABEL
Date: 20201229

ACTIVE INGREDIENTS: ISOPROPYL ALCOHOL 0.7 mL/1 mL
INACTIVE INGREDIENTS: WATER

Eco Chem isopropyl alcohol 70%

Active ingredient

Isopropyl alcohol 70%

Purpose

Antiseptic

Uses

- hand sanitizer to decrease bacteria on the skin
- recommended for repeated use
- for use when soap and water are not available

Warnings

Flammable keep away from fire/flame

For external use only.

Do not use

• in children less than 2 months of age
• on open skin wounds

When using this product

- do not get into eyes. In case of contact, rinse eyes thoroughly with water.

Stop use and ask a doctor if

- irritation or redness develop
- condition persists for more than 72 hours

Keep out of reach of children

- if swallowed get medical help or contact a Poison Control Center right away

Directions

- wet hands thoroughly with product and allow to dry without wiping
- supervise children under 6 years of age when using this product to avoid swallowing.

Other information

- Store between 15-30° C (59-86° F)
- avoid freezing and excessive heat above 40° C (104° F)
- may discolor some fabrics
- harmful to wood finishes and plastics

Inactive ingredients

- water

Questions?

1-787-477-4330

You may also report any serious side effects to this phone number. Mon-Fri 8:00AM-5:00PM